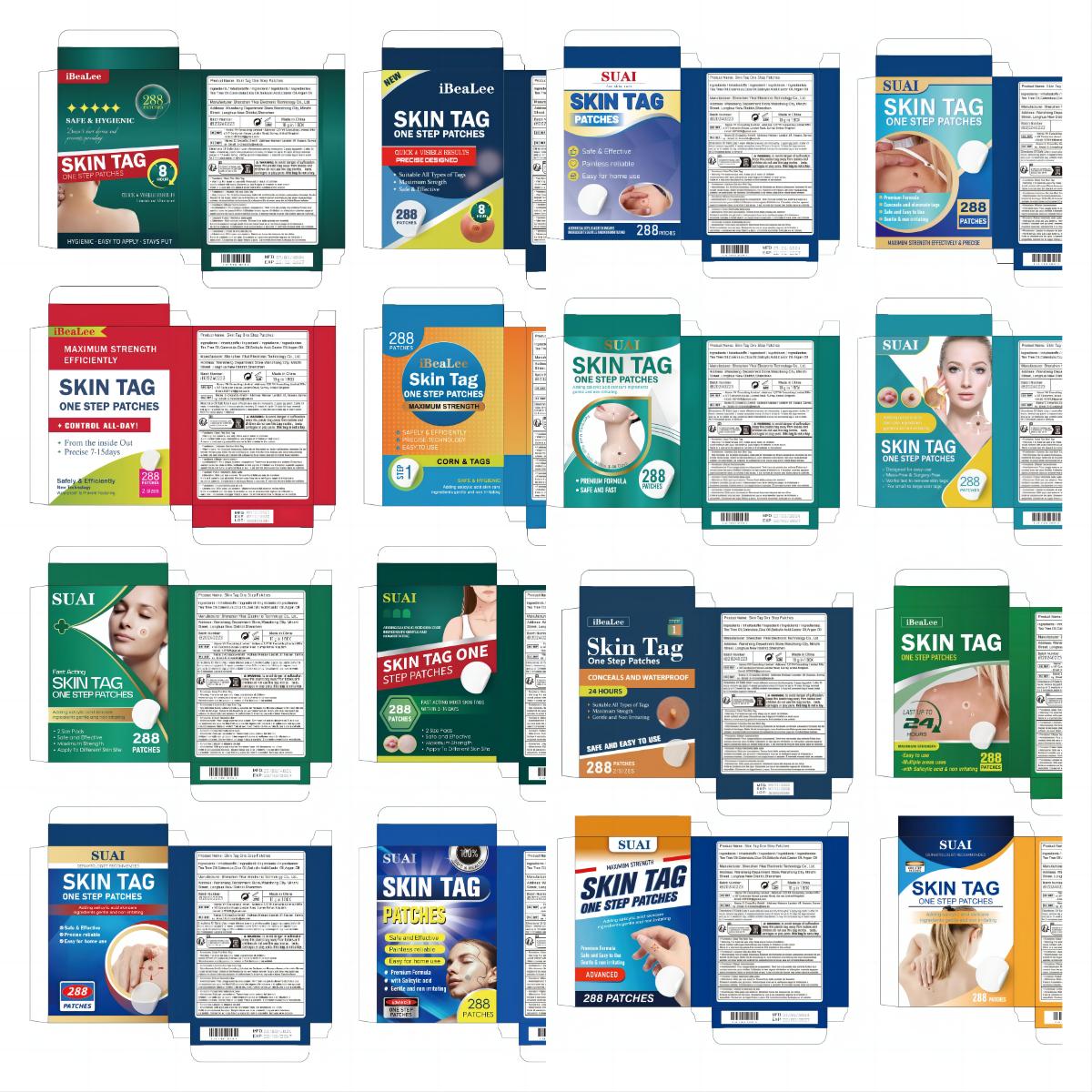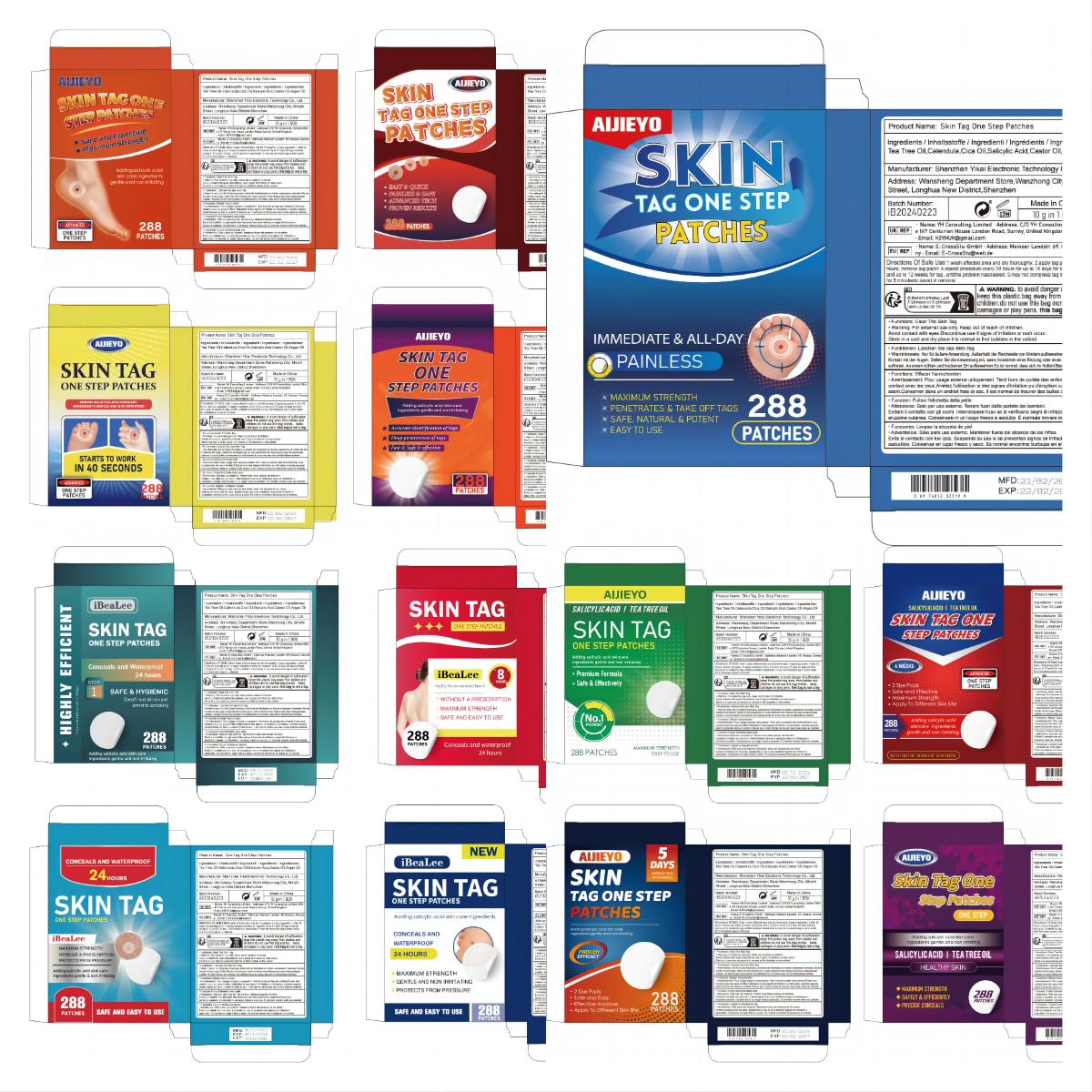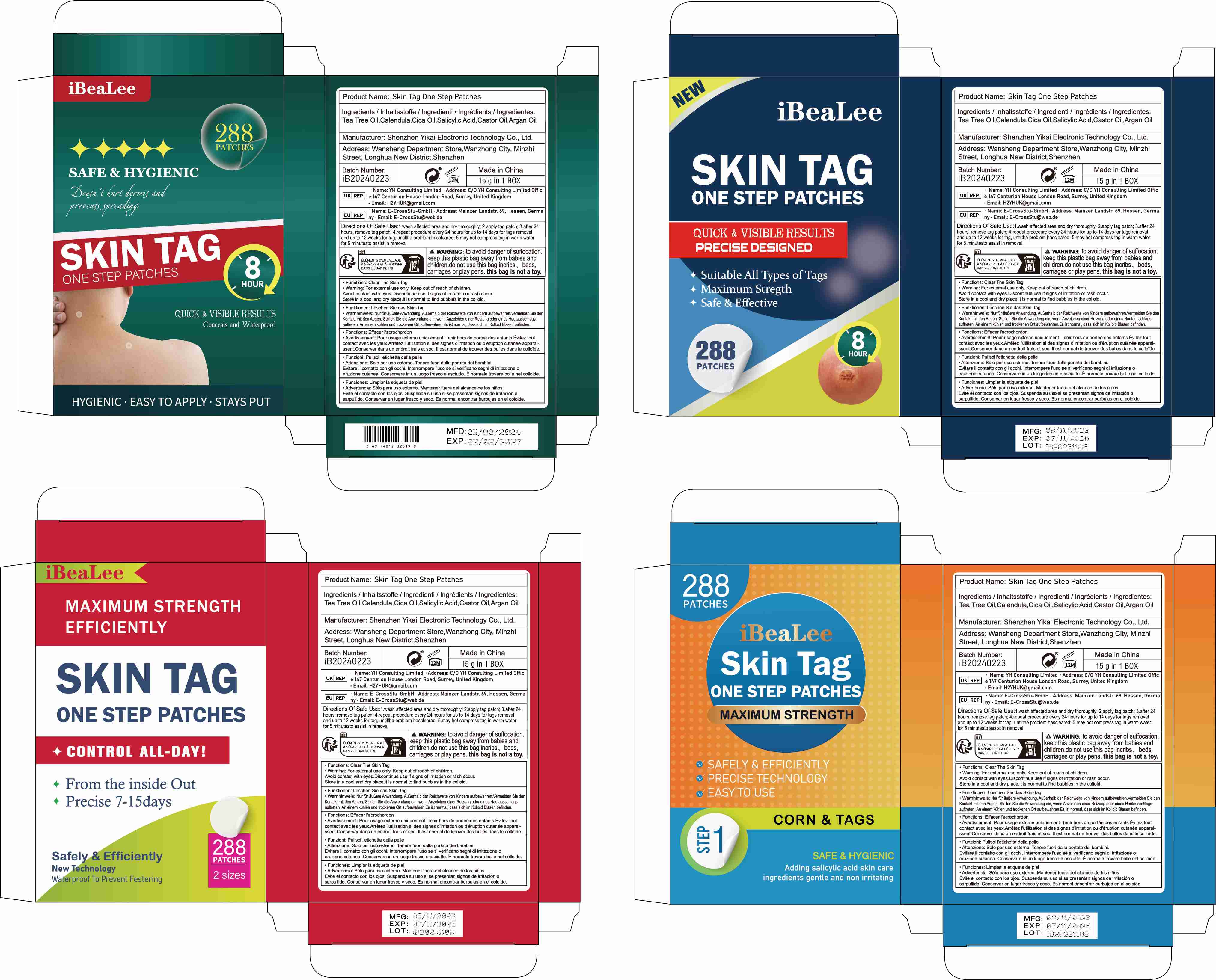 DRUG LABEL: Skin Tag One Step Patches
NDC: 83809-022 | Form: PATCH
Manufacturer: Shenzhen Yikai Electronic Technology Co., Ltd.
Category: otc | Type: HUMAN OTC DRUG LABEL
Date: 20240619

ACTIVE INGREDIENTS: SALICYLIC ACID 25 g/100 g
INACTIVE INGREDIENTS: TEA TREE OIL; CALENDULA ARVENSIS LEAF; OITICICA OIL; CASTOR OIL; ARGAN OIL

83809-022

Active Ingredient

Salicylic Acid 25%

Purpose

Wart remover

Use

Uses:for the removal of common and plantar warts
the common wart is easily recognized by the rough"cauliflower-like" appearance of the surface
the plantar wart is recognized by its location only on the bottom of the foot its tenderness and the interruption of the footprint pattern.

Warnings

Warnings: to avoid danger of suffocation.keep this plastic bag away from babies andchildren.do not use this bag incribs, beds carriages or play pens. this bag is not a toy.

Stop Use

Do not use: ● on irritated skin or on any area that is infected or reddenedon moles, birthmarks, warts with hair growing from them, warts on the face or mucous membranes

Keep Oot Of Reach Of Children

Directions

Directions Of Safe Use:

1.wash affected area and dry thoroughly;

2.apply tag patch;

3.after 24 hours, remove tag patch;

4.repeat procedure every 24 hours for up to 14 days for tags removal
and up to 12 weeks for tag, untilthe problem hascleared;

5.may hot compress tag in warm water for 5 minutesto assist in removal

Inactive ingredients

Tea Tree Oil,Calendula,Cica Oil,Castor Oil,Argan Oil